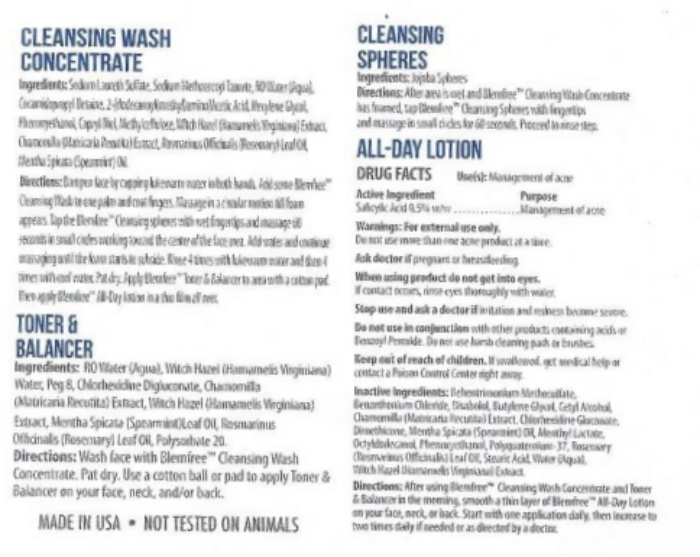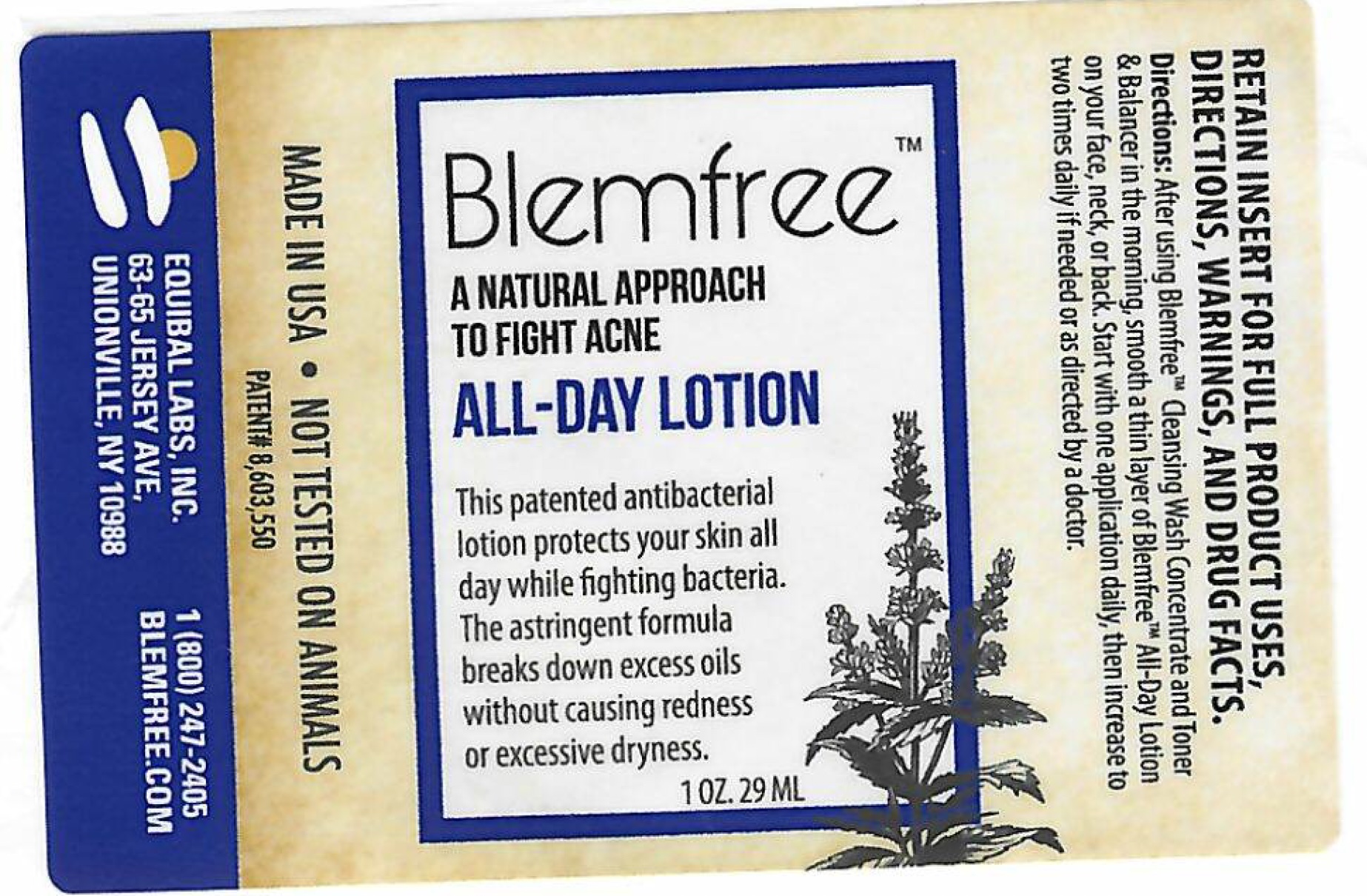 DRUG LABEL: Blemfree
NDC: 53228-003 | Form: LOTION
Manufacturer: Equibal, Inc.
Category: otc | Type: HUMAN OTC DRUG LABEL
Date: 20251217

ACTIVE INGREDIENTS: SALICYLIC ACID 1500 mg/29000 mg
INACTIVE INGREDIENTS: MENTHA SPICATA OIL

Blemfree All Day Lotion 1 oz

Active Ingredient

Salicylic Acid 5% w/w

Purpose

Management of Acne

Keep out of reach of children.If swallowed, get medical help or contact a Poison Control Center right away.

Indications and Usage

Management of Acne

Warnings

For external use only.

Do not use more than one acne product at a time.

Ask doctor

Ask doctor ifpregnant or breastfeeding.

When using

When using product do not get into eyes.

If contact occurs, rinse eyes thoroughly with water.

Stop Use

Stop use and ask a doctorif irritation and redness become severe.

Other Safety Information

Do not use in conjunctionwith other products containing acids or Benzoyl Peroxide. Do not use harsh cleaning pads or brushes.

Dosage & Administration

After area is wet with Blemfree™ Cleansing Wash Concentrate has foamed, tap Blemfree™ Cleansing Spheres with fingertips and massage in small circles for 60 seconds. Proceed to rinse step.

Inactive Ingredients

Behentrimonium Methosulfate, Benzethonium Chloride, Bisabolol, Butylene Glycol, Cetyl Alcohol, Chamomilla (matricaria Recutita) Extract, Chlorhexidine Gluconate, Dimethicone, Mentha Spicata (Spearmint) Oil, Menthyl Lactate, Octydodecanol, Phenoxyethhanol, Polyguatemium-37, Rosemary (Rosmarinus Officinalis) Leaf Oil, Stearic Acid, Water (Aqua), Witch Hazel (Hamamelis Virginiana) Extract.

Package Label

MADE IN USA●NOT TESTED ON ANIMALS

PATENT# 8,603,550

EQUIBAL LABS, INC. 1(800)247-2405

63-65 JERSEY AVE, BLEMFREE.COM

UNIONVILLE, NY 10988

Blemfree™

A NATURAL APPROACH TO FIGHT ACNE

ALL-DAY LOTION

This patented antibacterial lotion protects your skin all day while fighting bacteria. The astringent formula breaks down excess oils without causing redness or excessive dryness.

1 OZ. 29 ML

RETAIN INSERT FOR FULL PRODUCT USES, DIRECTIONS, WARNINGS, AND DRUG FACTS.

Directions:After using Blemfree™ Cleansing Wash Concentrate and Toner & Balancer in the morning, smooth a thin layer of Blemfree™ All-Day Lotion on your face, neck, or back. Start with one application daily, then increase to two times daily if needed or as directed by a doctor.

Blemfree All Day Lotion Package Insert

CLEANSING WASH CONCENTRATE

Ingredients:Sodium Laureth Sulfate, Sodium Methocoyl Taurate, RO Water (Aqua), Cocamidopropyl Betaine, 2- (dodecanoyl methyl) amino) Acetic Acid, Hexylene Glycol, Phenocyethanol, Capryl Diol, Methylcellulose, Witch Hazel (Hamamelis Virginiana) Extract, Chamomilla (Matricaria Recutita) Extract, Rosmarius Officnalis (Rosemary) Leaf Oil, Mentha Spicata (Spearmint) Oil.

Directions: Dampen face by cupping lukewarm water in both hands. Add some Blemfree™ Cleansing Wash to one palm and coat fingers. Massage in a circular motion till foam appears. Tap the Blemfree™ Cleansing spheres with wet fingertips and massage 60 seconds in small circles working toward the center of the face. Add water and continue massaging until the foam starts to subside. Rinse 4 times with lukewarm water and then 4 times with cool water. Pat dry. Apply Blemfree™ Toner & Balancer to area with a cotton pad. Then apply Blemfree™ All-Day Lotion in a thin film all over.

TONER & BALANCER

Ingredients:RO Water(Aqua), Witch Hazel (Hamamelis Virginiana) Water, Peg 8, chlorhexidine Digluconate, Chamomilla (Matricaria Recutita) Extract, Witch Hazel (Hamamelis Virginiana) Extract, Mentha Spicata (Spearmint) Leaf Oil, Rosmarinus Officinalis (Rosemary Leaf Oil, Polysorbate 20.

Directions:Wash face with Blemfree™ Cleansing Wash Concentrate, Pat dry. Use a cotton ball or pad to apply Tone & Balancer on your face, neck and/or back.

MADE IN USA ● NOT TESTED ON ANIMALS

CLEANSING SPHERES

Ingredients:Jojoba Spheres

Directions:After area is wet with Blemfree™ Cleansing Wash Concentrate has foamed, tap Blemfree™ Cleansing Spheres with fingertips and massage in small circles for 60 seconds. Proceed to rinse step.

ALL-DAY LOTION

DRUG FACTS Use(s): Management of acne

Active Ingredient Purpose

Salicylic Acid 0.5% w/w Management of acne

Warnings: For external use only.

Do not use more than one acne product at a time.

Ask doctor ifpregnant or breastfeeding.

When using product do not get into eyes.

If contact occurs, rinse eyes thoroughly with water.

Stop use and ask a doctorif irritation and redness become severe.

Do not use in conjunctionwith other products containing acids or Benzoyl Peroxide. Do not use harsh cleaning pads or brushes.

Keep out of reach of children.If swallowed, get medical help or contact a Poison Control Center right away.

Inactive Ingredients:Behentrimonium Methosulfate, Benzethonium Chloride, Bisabolol, Butylene Glycol, Cetyl Alcohol, Chamomilla (matricaria Recutita) Extract, Chlorhexidine Gluconate, Dimethicone, Mentha Spicata (Spearmint) Oil, Menthyl Lactate, Octydodecanol, Phenoxyethhanol, Polyguatemium-37, Rosemary (Rosmarinus Officinalis) Leaf Oil, Stearic Acid, Water (Aqua), Witch Hazel (Hamamelis Virginiana) Extract.

Directions:After using Blemfree™ Cleansing Wash Concentrate and Toner & Balancer in the morning, smooth a thin layer of Blemfree™ All-Day Lotion on your face, neck or back. Start with one application daily, then increase to two times daily if needed or as directed by a doctor.